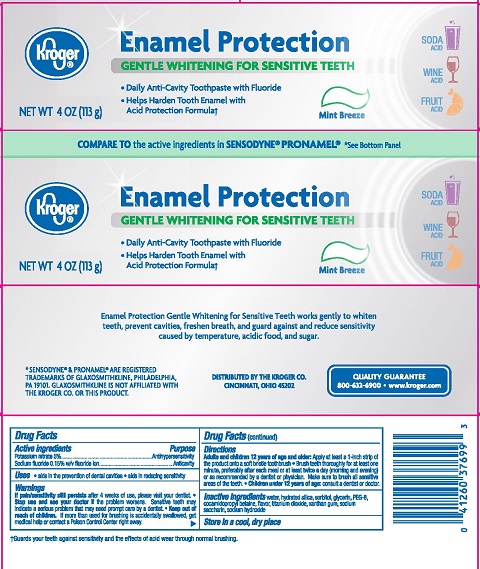 DRUG LABEL: Kroger Enamel Protection Sensitive
NDC: 30142-362 | Form: PASTE, DENTIFRICE
Manufacturer: Kroger Company
Category: otc | Type: HUMAN OTC DRUG LABEL
Date: 20251113

ACTIVE INGREDIENTS: POTASSIUM NITRATE 5 g/100 g; SODIUM FLUORIDE 0.15 g/100 g
INACTIVE INGREDIENTS: GLYCERIN; WATER; SACCHARIN SODIUM; SORBITOL; POLYETHYLENE GLYCOL, UNSPECIFIED; TITANIUM DIOXIDE; SODIUM HYDROXIDE; XANTHAN GUM; HYDRATED SILICA; COCAMIDOPROPYL BETAINE

5820255 Kroger Enamel Protection Sensitive Gentle Whitening

Drug Facts

Active ingredients

Potassium nitrate 5%

Sodium fluoride 0.15% w/v fluoride ion

Purpose

Antihypersensitivity

Anticavity

Uses

- aids in the prevention of dental cavities
- aids in reducing sensitivity

Warnings

WHEN USING

If pain/sensitivity still persists after 4 weeks of use, please visit your dentist.

Stop use and ask a dentist if the problem persists or worsens. Sensitive teeth may indicate a serious problem that may need prompt care by a dentist.

Keep out of reach of children. If more than used for brushing is accidentally swallowed, get medical help or contact a Poison Control Center right away.

Directions

Adults and children 12 years of age and older: Apply at least a 1-inch strip of the product onto a soft bristle toothbrush.

- Brush teeth thoroughly for at least one minute, preferably after each meal or at least twice a day (morning and evening) or as recommended by a dentist or physican. Make sure to brush all sensitive areas of the teeth
- Children under 12 years of age: consult a dentist or a doctor

INACTIVE INGREDIENT

Inactive ingredients water, hydrated silica, sorbitol,glycerin, PEG-8, cocamidopropyl betaine, flavor, titanium dioxide, xanthan gum, sodium saccharin, sodium hydroxide

STORAGE AND HANDLING

Store in a cool dry place

DISTRIBUTED BY THE KROGER CO.

CINCINNATI, OHIO 45202

QUALITY GUARANTEE

800-632-6900 • www.kroger.com

PACKAGE LABEL

Kroger® Enamel Protection

GENTLE WHITENING FOR SENSITIVE TEETH

- Daily Anti-cavity Toothpaste with Flouride
- Helps Harden Tooth Enamel with Acid Protection Formula

Mint Breeze

NET WT 4 OZ (113 g)